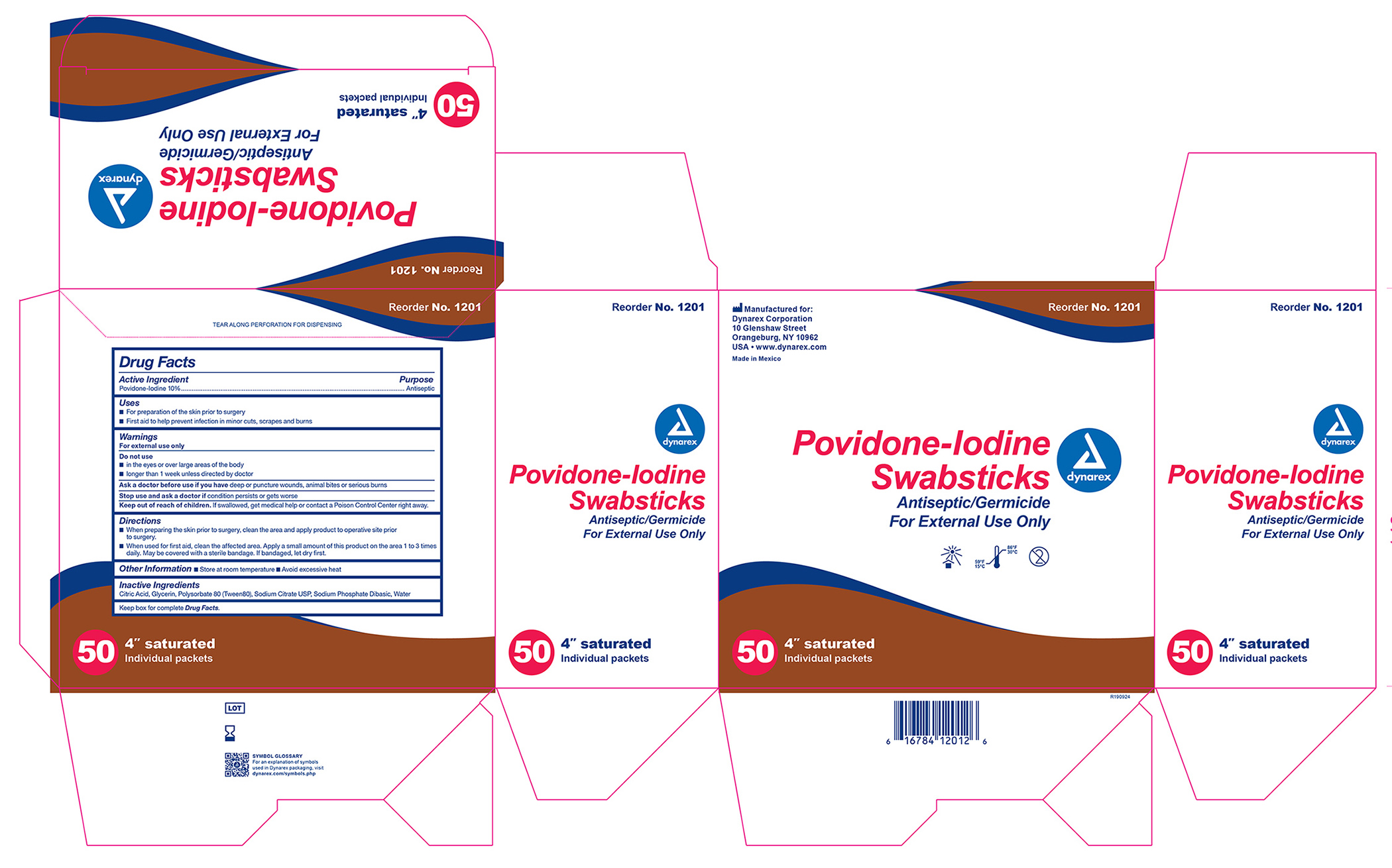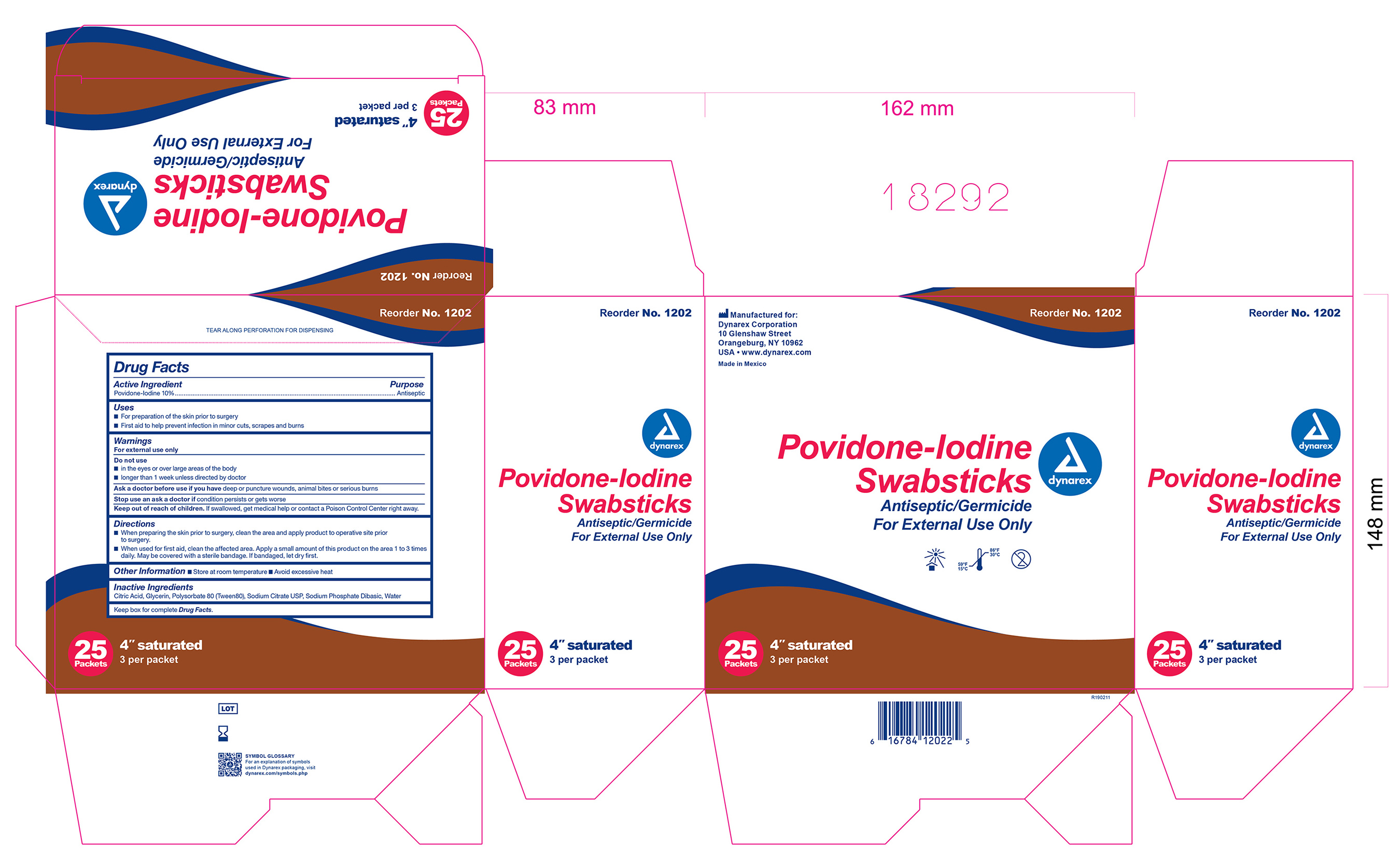 DRUG LABEL: povidine iodine
NDC: 67777-419 | Form: SWAB
Manufacturer: Dynarex Corporation
Category: otc | Type: HUMAN OTC DRUG LABEL
Date: 20251218

ACTIVE INGREDIENTS: POVIDONE-IODINE 10 mg/1 mL
INACTIVE INGREDIENTS: GLYCERIN; POLYSORBATE 80; SODIUM CITRATE; SODIUM PHOSPHATE, DIBASIC, ANHYDROUS; CITRIC ACID ACETATE; WATER

1201, 1202 Povidone Iodine Swabsticks

ACTIVE INGREDIENT

Section Text

Active Ingredient Purpose

Povidone Iodine 10% w/v (9.85% w/w/) Antiseptic

Purpose:

- First aid antiseptic to help prevent skin infection in minor cuts, scrapes and burns.
- For preparation of the skin prior to surgery.
- Helps reduce bacteria that can potentially cause skin infections.

Warnings:

Section Text

- FOR EXTERNAL USE ONLY

Do not use:

- As a first aid antiseptic for more than 1 week.
- In the eyes.
- Over large areas of the body.

Ask a doctor before use if you have:

- Deep puncture wounds
- Animal bites
- Serious burns

Stop Use:

- If irritation and redness develop
- If condition persists for more than 72 hours, consult a physician.

Keep out of reach of children.If swallowed, get medical help or contact a Poison Control Center.

Directions Povidone iodine:

Tear at notch, remove applicator, use only once.

As a first aid antiseptic

- clean affected area
- apply 1 to 3 times daily
- may be covered with a sterile bandage, if bandaged let dry.

For preoperative patient skin preparation

- clean area
- apply to operative site prior to surgery using the applicator

Other information:

Store at room temperature.

Avoid excessive heat

INDICATIONS AND USAGE

For use as an

- first aid antiseptic
- pre-operative skin preperation

Inactive Ingredients

Inactive ingredients: Citric acid, glycerin, polysorbate 80, sodium citrate USP, sodium phosphate dibasic, water

Principal Display Panel

Povidone Iodine Swabsticks 1201 & 1202

PVP 419.jpg